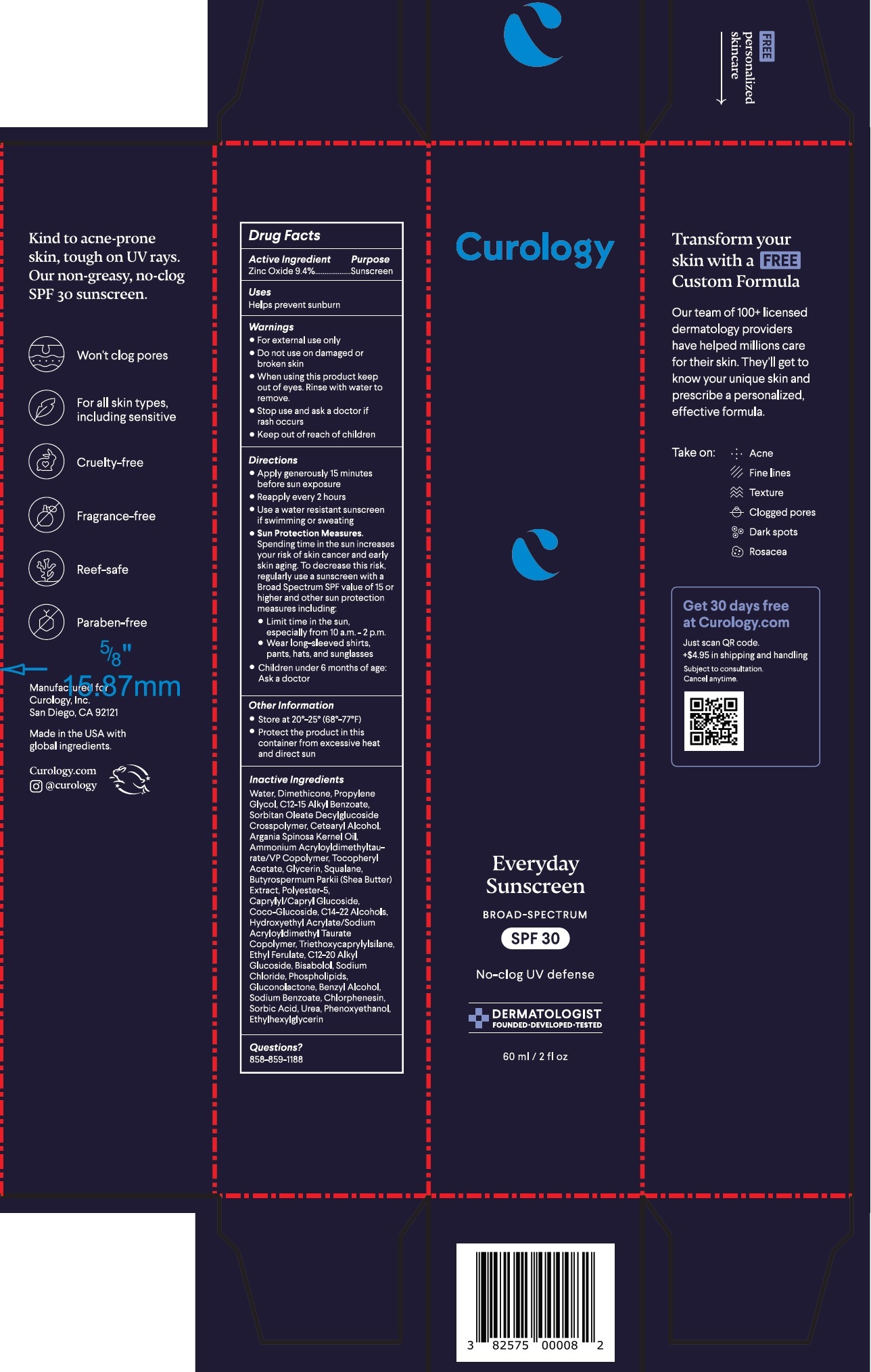 DRUG LABEL: Curology Everyday Sunscreen Broad Spectrum SPF 30 No-clog UV defense
NDC: 82575-035 | Form: CREAM
Manufacturer: Curology
Category: otc | Type: HUMAN OTC DRUG LABEL
Date: 20251015

ACTIVE INGREDIENTS: ZINC OXIDE 94 mg/1 mL
INACTIVE INGREDIENTS: WATER; DIMETHICONE; PROPYLENE GLYCOL; ALKYL (C12-15) BENZOATE; CETOSTEARYL ALCOHOL; ARGAN OIL; AMMONIUM ACRYLOYLDIMETHYLTAURATE/VP COPOLYMER; .ALPHA.-TOCOPHEROL ACETATE; GLYCERIN; SQUALANE; SHEA BUTTER; CAPRYLYL/CAPRYL OLIGOGLUCOSIDE; COCO GLUCOSIDE; C14-22 ALCOHOLS; TRIETHOXYCAPRYLYLSILANE; ETHYL FERULATE; C12-20 ALKYL GLUCOSIDE; LEVOMENOL; SODIUM CHLORIDE; GLUCONOLACTONE; BENZYL ALCOHOL; SODIUM BENZOATE; CHLORPHENESIN; SORBIC ACID; UREA; PHENOXYETHANOL; ETHYLHEXYLGLYCERIN

Curology Everyday Sunscreen Broad Spectrum SPF 30 No-clog UV defense

Active Ingredient

Zinc Oxide 9.4%

Purpose

Sunscreen

Uses

Helps prevent sunburn

Warnings

- For external use only

Do not use

- on damaged or broken skin

When using this product

- keep out of eyes. Rinse with water to remove.

Stop use and ask a doctor

- if rash occurs

Directions

- Apply gernerously 15 minutes before sun exposure
- Reapply every 2 hours
- Use a water resistant sunscreen if swimming or sweating
- Spending time in the sun increases your risk of skin cancer and early skin aging. To decrease this risk, regularly use a sunscreen with a Broad Spectrum SPF value of 15 or higher and other sun protection measures including: Sun Protection Measures.
- Limit time in the sun, especially from 10 a.m.-2 p.m.
- Wear long-sleeved shirts, pants, hats, and sunglasses
- Children under 6 months of age: Ask a doctor

Other Information

- Store at 20°-25° (68°-77°F)
- Protect the product in this container from excessive heat and direct sun

Inactive Ingredients

Water, Dimethicone, Propylene Glycol, C12-15 Alkyl Benzoate, Sorbitan Oleate Decylglucoside Crosspolymer, Cetearyl Alcohol, Argania Spinosa Kernel Oil, Ammonium Acryloyldimethyltaurate/VP Copolymer, Tocopheryl Acetate, Glycerin, Squalane, Butyrospermum Parkii (Shea Butter) Extract, Polyester-5, Caprylyl/Capryl Glucoside, Coco-Glucoside, C14-22 Alcohols, Hydroxyethyl Acrylate/Sodium Acryloyldimethyl Taurate Copolymer, Triethoxycaprylylsilane, Ethyl Ferulate, C12-20 Alkyl Glucoside, Bisabolol, Sodium Chloride, Phospholipids, Gluconolactone, Benzyl Alcohol, Sodium Benzoate, Chlorphenesin, Sorbic Acid, Urea, Phenoxyethanol, Ethylhexylglycerin

Questions?

858-859-1188